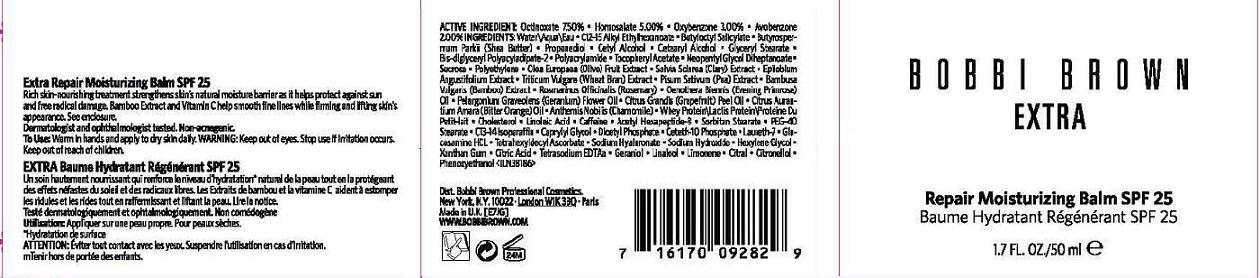 DRUG LABEL: EXTRA
NDC: 64141-112 | Form: CREAM
Manufacturer: Bobbi Brown Professional Cosmetics Inc.
Category: otc | Type: HUMAN OTC DRUG LABEL
Date: 20110919

ACTIVE INGREDIENTS: OCTINOXATE 7.5 mL/100 mL; HOMOSALATE 5.0 mL/100 mL; OXYBENZONE 3.0 mL/100 mL; AVOBENZONE 2.0 mL/100 mL
INACTIVE INGREDIENTS: WATER; BUTYLOCTYL SALICYLATE; SHEA BUTTER; PROPANEDIOL; CETYL ALCOHOL; CETOSTEARYL ALCOHOL; GLYCERYL MONOSTEARATE; ALPHA-TOCOPHEROL ACETATE; NEOPENTYL GLYCOL DIHEPTANOATE; SUCROSE; HIGH DENSITY POLYETHYLENE; BLACK OLIVE; CLARY SAGE; EPILOBIUM ANGUSTIFOLIUM FLOWERING TOP; WHEAT BRAN; PEA; BAMBUSA VULGARIS TOP; ROSEMARY; EVENING PRIMROSE OIL; PELARGONIUM GRAVEOLENS FLOWERING TOP; CITRUS MAXIMA FRUIT RIND; CITRUS AURANTIUM FLOWER OIL; CHAMAEMELUM NOBILE; WHEY; CHOLESTEROL; LINOLEIC ACID; CAFFEINE; ACETYL HEXAPEPTIDE-3; SORBITAN MONOSTEARATE; PEG-40 STEARATE; C13-14 ISOPARAFFIN; CAPRYLYL GLYCOL; DIHEXADECYL PHOSPHATE; CETETH-10 PHOSPHATE; LAURETH-7; GLUCOSAMINE HYDROCHLORIDE; HYALURONATE SODIUM; SODIUM HYDROXIDE; HEXYLENE GLYCOL; XANTHAN GUM; CITRIC ACID MONOHYDRATE; EDETATE SODIUM; PHENOXYETHANOL

ACTIVE INGREDIENT

ACTIVE INGREDIENTS: OCTINOXATE 7.50% [] HOMOSALATE 5.00% [] OXYBENZONE 3.00% [] AVOBENZONE 2.00%

INACTIVE INGREDIENT

INACTIVE INGREDIENTS: WATER [] C12-15 ALKYL ETHYLHEXANOATE [] BUTYLOCTYL SALICYLATE [] BUTYROSPERMUM PARKII (SHEA BUTTER) [] PROPANEDIOL [] CETYL ALCOHOL [] CETEARYL ALCOHOL [] GLYCERYL STEARATE [] BIS-DIGLYCERYL POLYACYLADIPATE-2 [] POLYACRYLAMIDE [] TOCOPHERYL ACETATE [] NEOPENTYL GLYCOL DIHEPTANOATE [] SUCROSE [] POLYETHYLENE [] OLEA EUROPAEA (OLIVE) FRUIT EXTRACT [] SALVIA SCLAREA (CLARY) EXTRACT [] EPILOBIUM ANGUSTIFOLIUM EXTRACT [] TRITICUM VULGARE (WHEAT BRAN) EXTRACT [] PISUM SATIVUM (PEA) EXTRACT [] BAMBUSA VULGARIS (BAMBOO) EXTRACT [] ROSMARINUS OFFICINALIS (ROSEMARY) [] OENOTHERA BIENNIS (EVENING PRIMROSE) OIL [] PELARGONIUM GRAVEOLENS (GERANIUM) FLOWER OIL [] CITRUS GRANDIS (GRAPEFRUIT) PEEL OIL [] CITRUS AURANTIUM AMARA (BITTER ORANGE) OIL [] ANTHEMIS NOBILIS (CHAMOMILE) [] WHEY PROTEIN\LACTIS PROTEIN\PROTEINE DU PETIT-LAIT [] CHOLESTEROL [] LINOLEIC ACID [] CAFFEINE [] ACETYL HEXAPEPTIDE-8 [] SORBITAN STEARATE [] PEG-40 STEARATE [] C13-14 ISOPARAFFIN [] CAPRYLYL GLYCOL [] DICETYL PHOSPHATE [] CETETH-10 PHOSPHATE [] LAURETH-7 [] GLUCOSAMINE HCL [] TETRAHEXYLDECYL ASCORBATE [] SODIUM HYALURONATE [] SODIUM HYDROXIDE [] HEXYLENE GLYCOL [] XANTHAN GUM [] CITRIC ACID [] TETRASODIUM EDTA [] GERANIOL [] LINALOOL [] LIMONENE [] CITRAL [] CITRONELLOL [] PHENOXYETHANOL

WARNINGS

WARNING: KEEP OUT OF EYES. STOP USE IF IRRITATION OCCURS. KEEP OUT OF REACH OF CHILDREN.

PACKAGE LABEL

BOBBI BROWN

EXTRA

REPAIR MOISTURIZING

BALM SPF 25

1.7 OZ./50 ML

DISTR. BOBBI BROWN PROFESSIONAL COSMETICS

NEW YORK, NY 10022